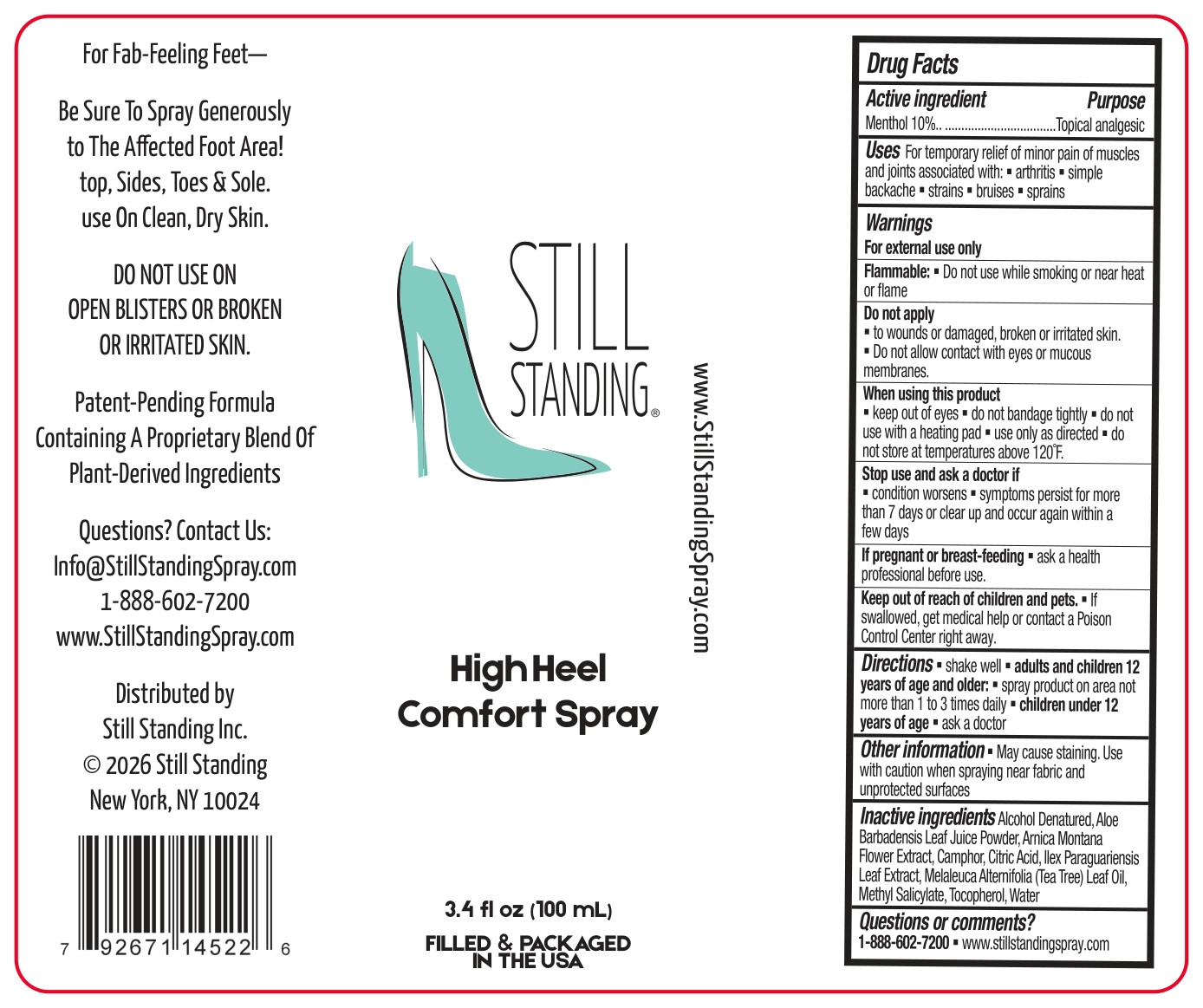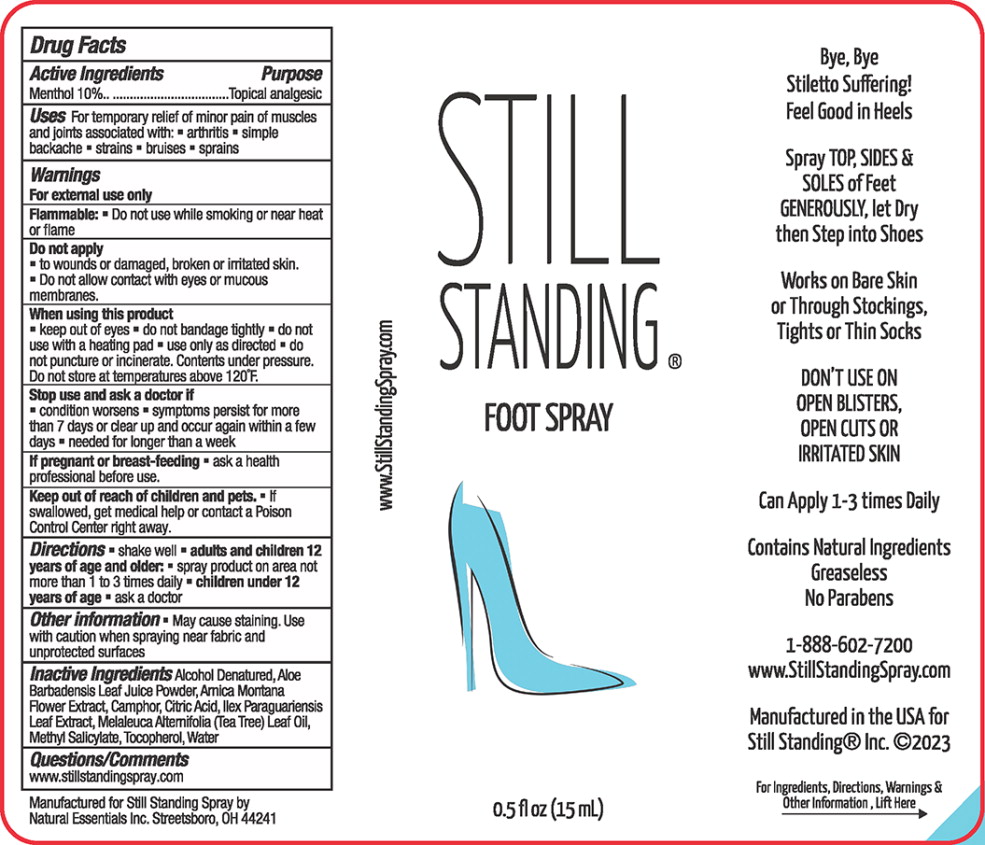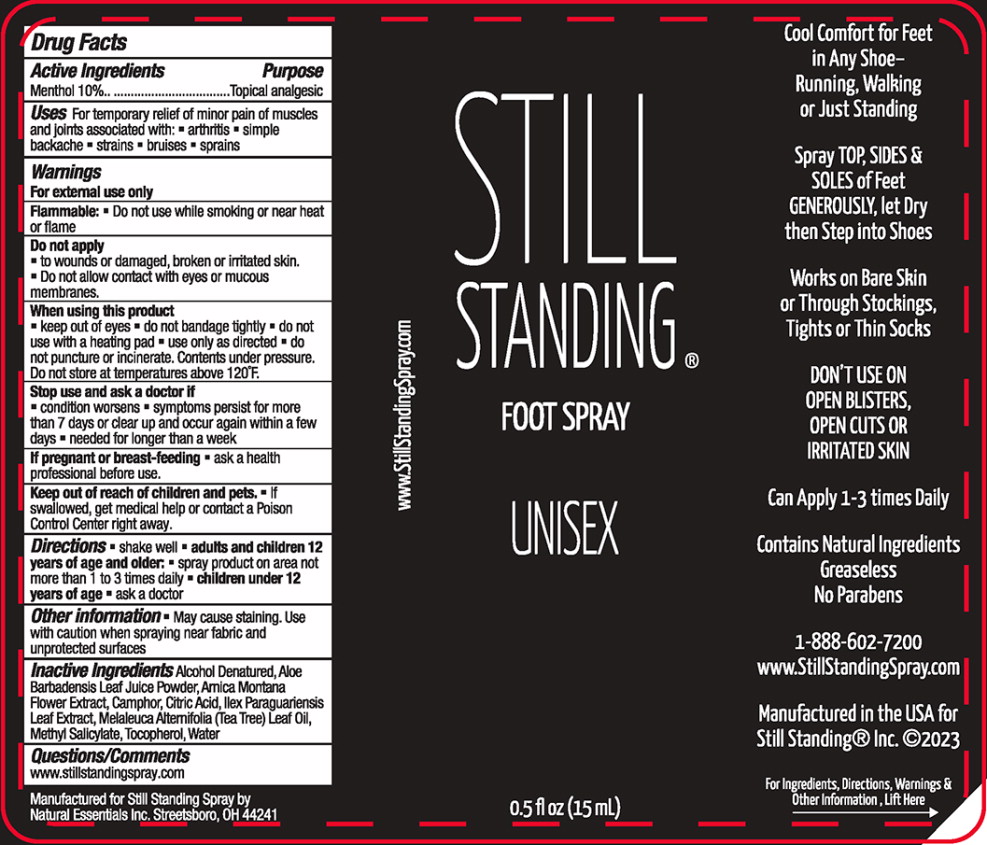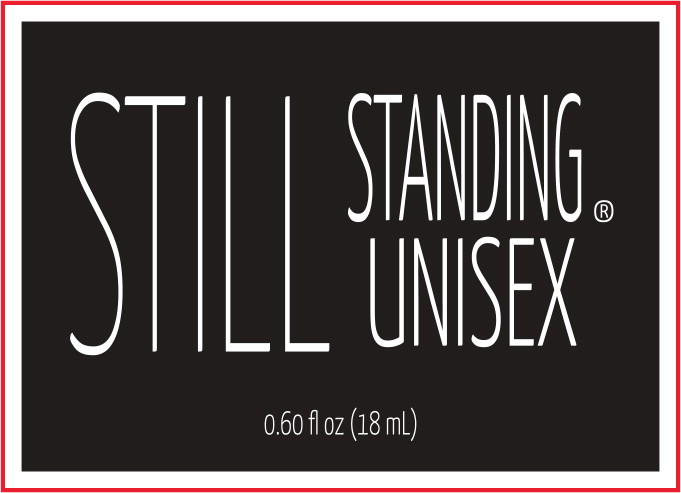 DRUG LABEL: Still Standing
NDC: 66902-167 | Form: LIQUID
Manufacturer: Natural Essentials Inc.
Category: otc | Type: HUMAN OTC DRUG LABEL
Date: 20260302

ACTIVE INGREDIENTS: MENTHOL, UNSPECIFIED FORM 100 mg/1 mL
INACTIVE INGREDIENTS: ALCOHOL; ALOE VERA LEAF; ARNICA MONTANA FLOWER; CAMPHOR (SYNTHETIC); CITRIC ACID MONOHYDRATE; .ALPHA.-TOCOPHEROL ACETATE; ILEX PARAGUARIENSIS LEAF; METHYL SALICYLATE; TEA TREE OIL; WATER

Drug Facts

Active Ingredients

Menthol 10%

Purpose

Topical analgesic

Uses

For temporary relief of minor pain of muscles and joints associated with:

- arthritis
- simple backache
- strains
- bruises
- sprains

Warnings

For external use only

Flammable:

- Do not use while smoking or near heat or flame

Do not apply

- to wounds or damaged, broken or irritated skin.
- Do not allow contact with eyes or mucous membranes.

When using this product

- keep out of eyes
- do not bandage tightly
- do not use with a heating pad
- use only as directed
- do not puncture or incinerate. Contents under pressure. Do not store at temperatures above 120°F.

Stop use and ask a doctor if

- condition worsens
- symptoms persist for more than 7 days or dear up and occur again within a few days
- needed for longer than a week

If pregnant or breast-feeding

- ask a health professional before use.

Keep out of reach of children and pets.

- If swallowed, get medical help or contact a Poison Control Center right away.

Directions

- shake well
- adults and children 12 years of age and olden
- spray product on area not more than 1 to 3 times daily
- children under 12 years of age ■ask a doctor

Other information

- May cause staining. Use with caution when spraying near fabric and unprotected surfaces

Inactive Ingredients

Alcohol Denatured, Aloe Barbadensis Leaf Juice Powder, Arnica Montana Flower Extract, Camphor, Citric Acid, Ilex Paraguariensis Leaf Extract, Melaleuca Altemifolia (Tea Tree) Leaf Oil, Methyl Salicylate, Tocopherol, Water

Questions/Comments

www.stillstandingspray.com

Principal Display Panel – 15 mL Bottle Spray Label

STILL
STANDING®

FOOT SPRAY

0.5 fl oz (15 mL)

Principal Display Panel – 15 mL Bottle Spray Label

STILL
STANDING®

FOOT SPRAY

UNISEX

0.5 fl oz (15 mL)

Principal Display Panel – 18 mL Bottle Spray Label

STILL
STANDING

UNISEX®

0.60 fl oz (18 mL)

Principal Display Panel - 100 mL Bottle

STILL STANDING®

High Heel

Comfort Spray

3.4 fl oz (100 mL)

Filled & Packaged

in the USA

www.StillStandingSpray.com